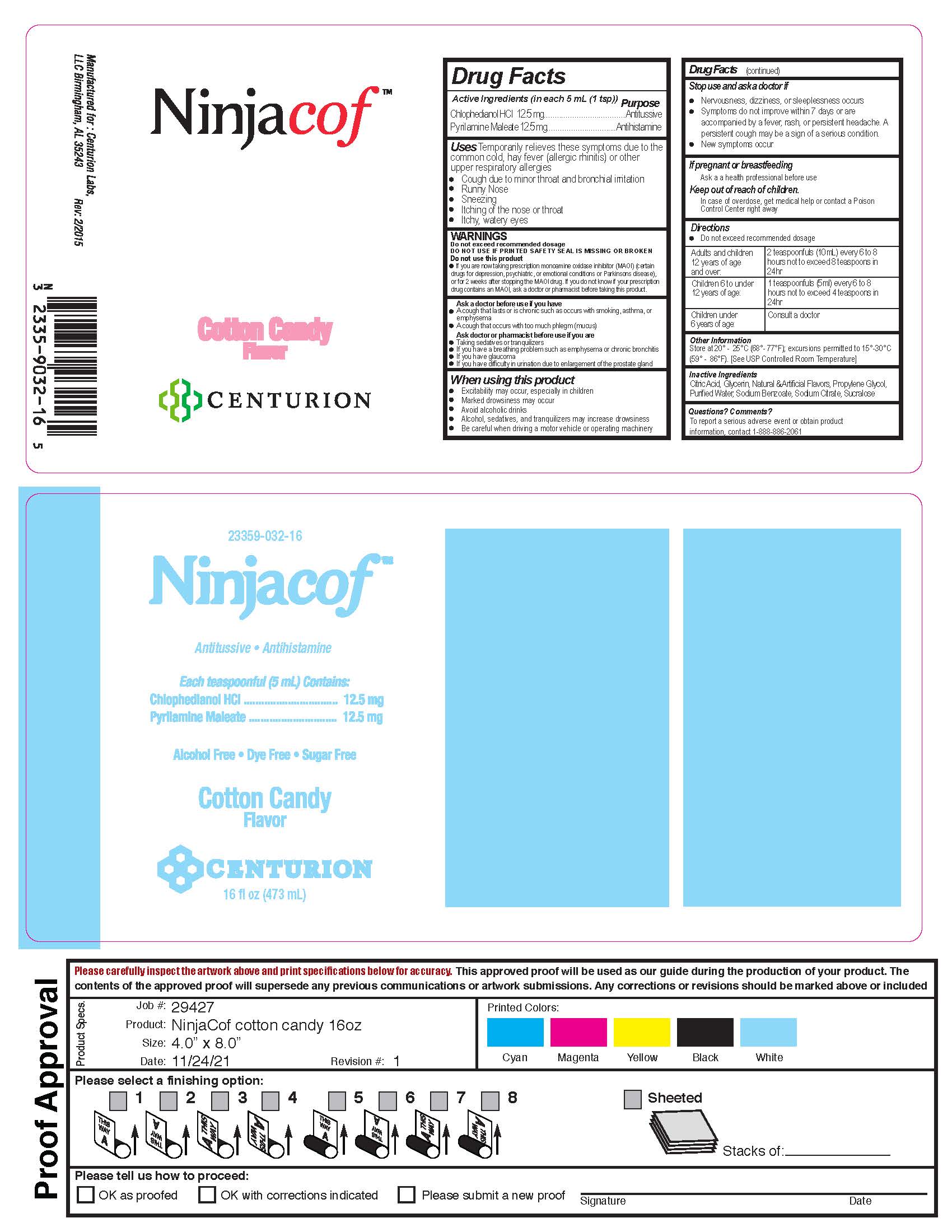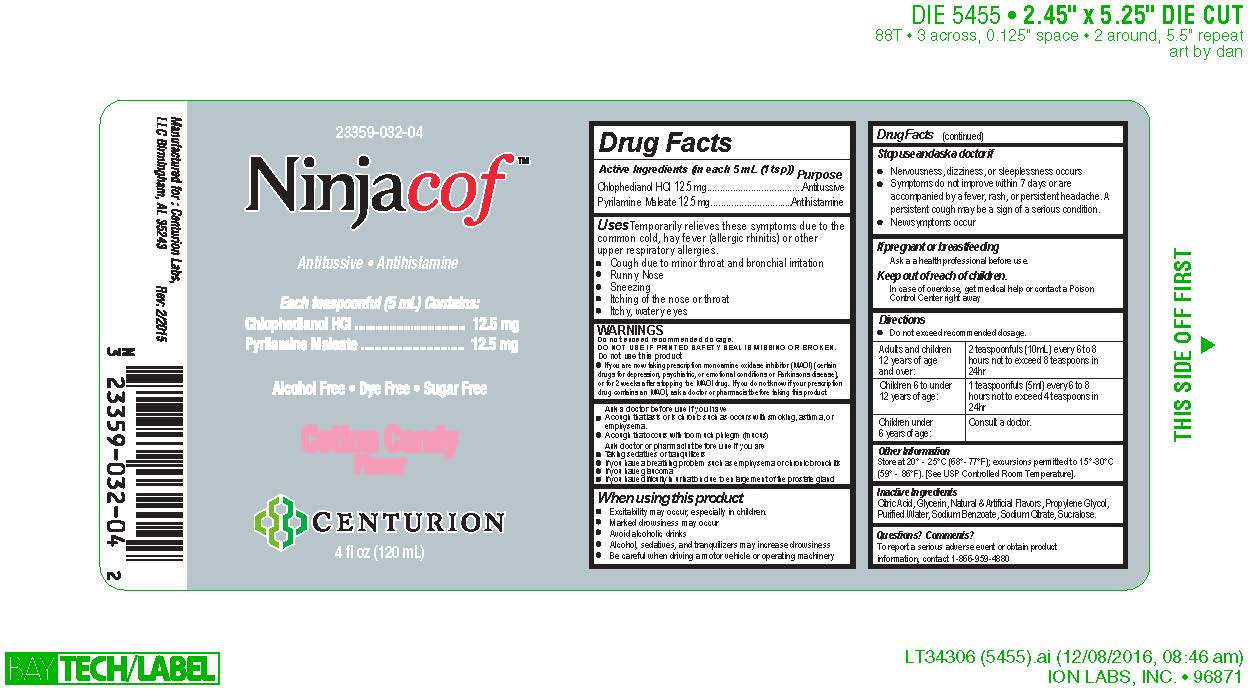 DRUG LABEL: Ninjacof Cotton Candy Flavor- 16 oz
NDC: 79804-032 | Form: LIQUID
Manufacturer: Eagle Labs Inc.
Category: otc | Type: HUMAN OTC DRUG LABEL
Date: 20240415

ACTIVE INGREDIENTS: PYRILAMINE MALEATE 12.5 mg/5 mL; CHLOPHEDIANOL HYDROCHLORIDE 12.5 mg/5 mL
INACTIVE INGREDIENTS: SUCRALOSE; SODIUM CITRATE; WATER; SODIUM BENZOATE; CITRIC ACID MONOHYDRATE; PROPYLENE GLYCOL

Ninjacof Cotton Candy Flavor

Active Ingredient

Chlophedianol HCL

Pryilamine Maleate

Purpose

Anitussive

Antihistamine

USES

Temporarily relieves these symptoms due to the common cold, hayfever, (allergic rhinitis) or other upper respiratroy allergies.

Cough due to minor throat and bronchial irritation
Runny Nose
Sneezing
Itching of the Nose or Throat
Itchy, watery eyes

Warnings

Do not exceed recommended dosage.
DO NOT USE IF PRINTED SAFETY SEAL IS MISSING OR BROKEN.
Do not use this product
If you are now taking prescription monoamine oxidase inhibitor (MAOI) (certain
drugs for depression, psychiatric, or emotional conditions or Parkinsons disease),
or for 2 weeks after stopping the MAOI drug. If you do not know if your prescription
drug contains an MAOI, ask a doctor or pharmacist before taking this product.

Ask a doctor before use if you have

A cough that lasts or is chronic such as occurs with smoking, asthma, or
emphysema.
A cough that occurs with too much phlegm (mucus)
Ask doctor or pharmacist before use if you are
Taking sedatives or tranquilizers
If you have a breathing problem such as emphysema or chronic bronchitis
If you have glaucoma
If you have difficulty in urination due to enlargement of the prostate gland

When using this product

Excitability may occur, especially in children.
Marked drowsiness may occur
Avoid alcoholic drinks
Alcohol, sedatives, and tranquilizers may increase drowsiness
Be careful when driving a motor vehicle or operating machinery

Stop use and ask a doctor if

Nervousness, dizziness, or sleeplessness occurs
Symptoms do not improve within 7 days or are
accompanied by a fever, rash, or persistent headache. A
persistent cough may be a sign of a serious condition.
New symptoms occur

Keep out of reach of children

In case of overdose, get medical help or contact a Poison
Control Center right away

Directions

Do not exceed recommended dosage.
In case of overdose, get medical help or contact a Poison
Control Center right away

Adults and children
12 years of age
and over: 2 teaspoonfuls (10mL) every 6 to 8
hours not to exceed 8 teaspoons in
24hr

Children 6 to under
12 years of age:1 teaspoonfuls (5ml) every 6 to 8
hours not to exceed 4 teaspoons in
24hr

Children under
6 years of age: Consult a doctor.

Other

Store at 20° - 25°C (68°- 77°F); excursions permitted to 15°-30°C
(59° - 86°F). [See USP Controlled Room Temperature].

Inactive Ingredients

Citric Acid, Glycerin, Natural & Artificial Flavors, Propylene Glycol,
Purified Water, Sodium Benzoate, Sodium Citrate, Sucralose

Questions? Comments?

To report a serious adverse event or obtain product
information, contact 1-866-959-4880